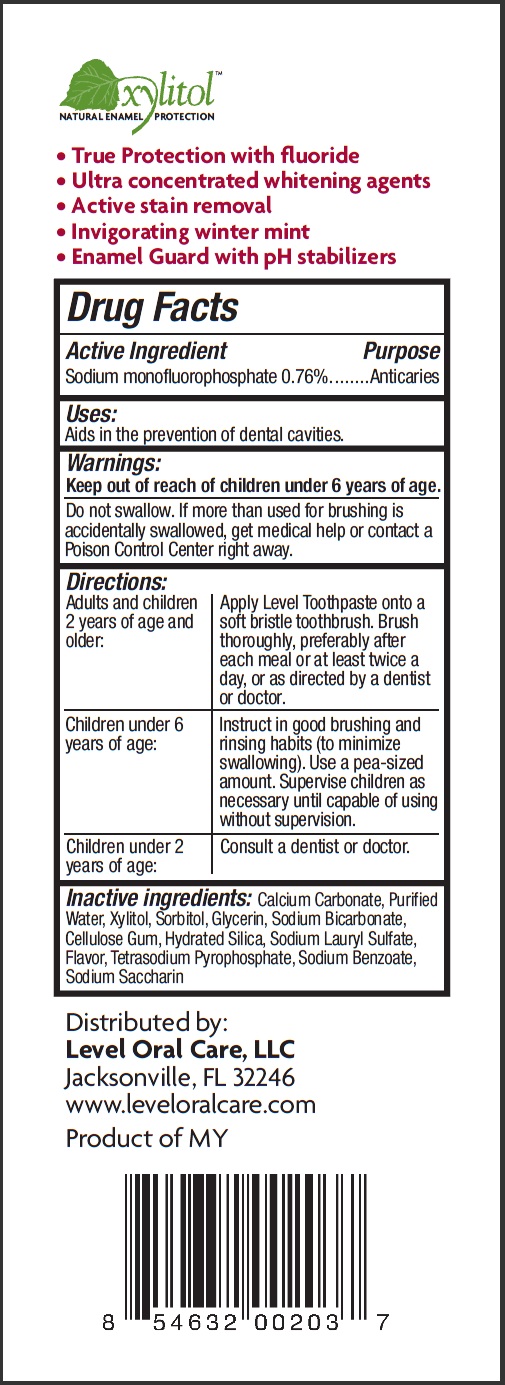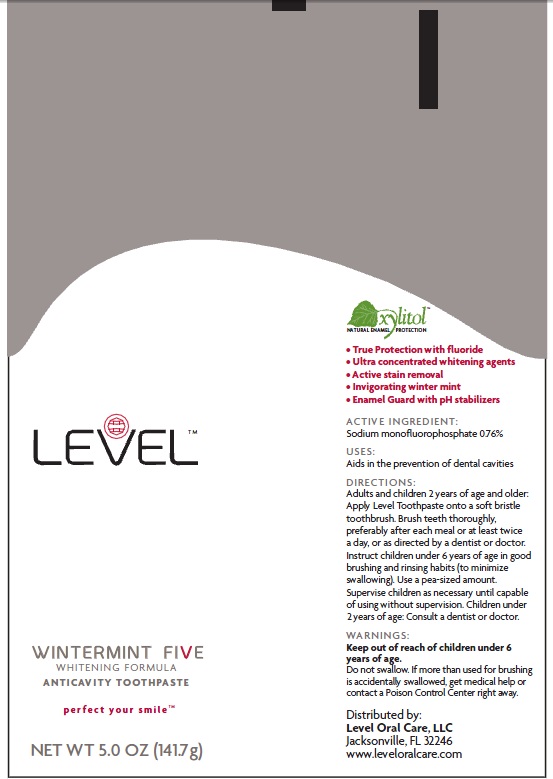 DRUG LABEL: LEVEL WINTERMINT FIVE WHITENING FORMULA ANTICAVITY 
NDC: 50001-121 | Form: PASTE
Manufacturer: LEVEL ORAL CARE, LLC
Category: otc | Type: HUMAN OTC DRUG LABEL
Date: 20110509

ACTIVE INGREDIENTS: SODIUM MONOFLUOROPHOSPHATE 0.76 g/100 g
INACTIVE INGREDIENTS: CALCIUM CARBONATE; WATER; XYLITOL; SORBITOL; GLYCERIN; SODIUM BICARBONATE; CARBOXYMETHYLCELLULOSE SODIUM; HYDRATED SILICA; SODIUM LAURYL SULFATE; SODIUM PYROPHOSPHATE; SODIUM BENZOATE; SACCHARIN SODIUM

LEVEL WINTERMINT FIVE WHITENING FORMULA ANTICAVITY TOOTHPASTE perfect your smile

DRUG FACTS
Active Ingredient Purpose
Sodium Monofluorophosphate 0.76%....Anticaries

Purpose
Anticaries

Uses:
Aids in the prevention of dental cavities.

WARNING

Do not swallow. If more than used for brushing is accidentally swallowed, get medical help or contact a Poison control Center right away.

Keep out of reach of children under 6 years of age.

DIRECTIONS
Adults and children 2 years of age and older:
Apply Level Toothpaste on to a soft bristle toothbrush. Brush thoroughly, preferably after each meal or at least twice a day or as directed by a dentist or doctor
Children under 6 years of age
Instruct in good brushing and rinsing habits (to minimize swallowing). Use a pea-sized amount. Supervise children as necessary until capable of using without supervision.
Children under 2 years of age:
consult a dentist or doctor

Inactive Ingredients
Calcium Carbonate, Purified Water, Xylitol, Sorbitol, Glycerin, Sodium Bicarbonate, Cellulose Gum, Hydrated Silica, Sodium Lauryl Sulfate, Flavor, Tetrasodium Pyrophosphate, Sodium Benzoate, Sodium Saccharin

Xylitol
Natural Enamel protection
True protection with fluoride
Ultra concentrated whitening agents
Active stain removal
Invigorating winter mint
enamel guard with pH stabilizers
Distributed by
Level Oral Care, LLC
Jacksonville, FL 32246
www.leveloralcare.com
Product of MY

PACKAGE LABEL

Level
Wintermint Five
Whitening Formula
Anticavity Toothpaste
perfect your smile
NET WT. 5.0 OZ (141.7G)
Xylitol
natural enamel protection
True protection with fluoride
Ultra concentrated whitening agents
Active stain removal
Invigorating winter mint
Enamel Guard with pH stabilizers
ACTIVE INGREDIENT:
Sodium monofluorophosphate 0.76%
USES:
Aids in the prevention of dental cavities
DIRECTIONS:
Adults and children 2 years of age and older: Apply Level Toothpaste onto a soft bristle toothbrush. Brush teeth thoroughly, preferably after each meal or at least twice a day, or as directed by a dentist or doctor. Instruct children under 6 years of age in good brushing and rinsing habits (to minimize swallowing). Use a pea-sized amount. supervise children as necessary until capable of using without supervision. Children under 2 years of age: Consult a dentist or doctor
WARNINGS
Keep out of reach of children under 6 years of age. Do not swallow. if more than used from brushing is accidentally swallowed, get medical help or contact a Poison Control Center right away.
Distributed by:
Level Oral Care, LLC
Jacksonville, FL 32246
www.leveloralcare.com